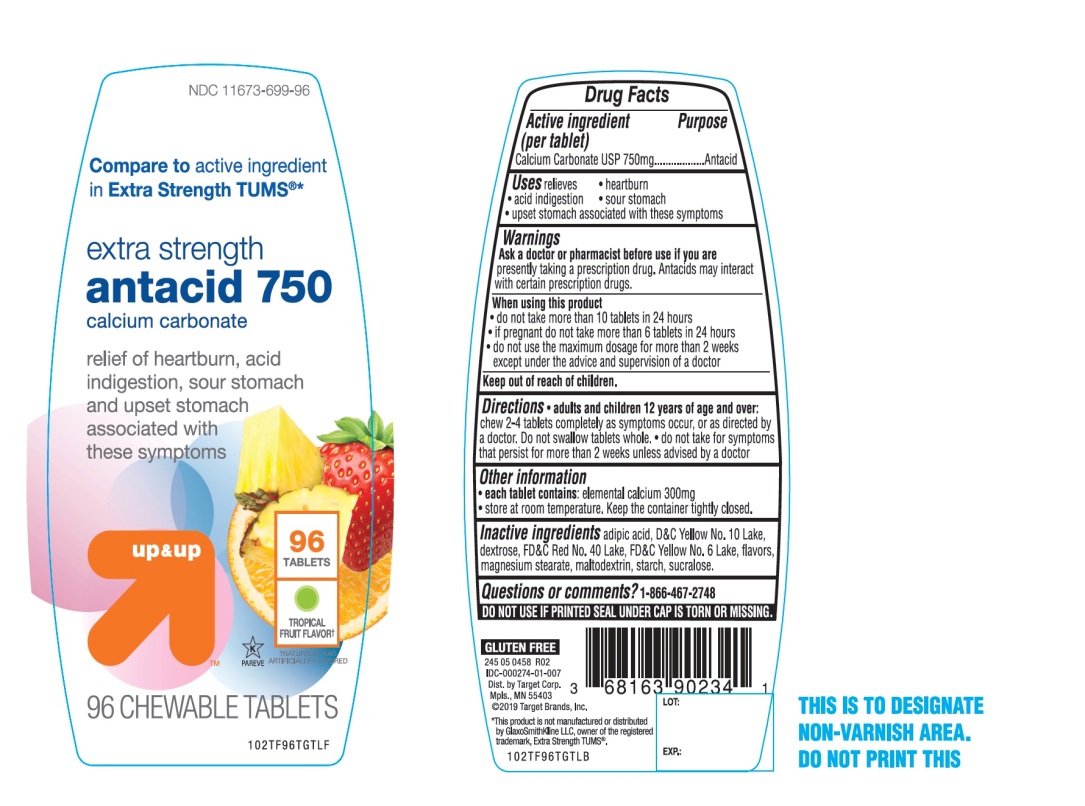 DRUG LABEL: extra strength

NDC: 11673-699 | Form: TABLET, CHEWABLE
Manufacturer: Target Corporation
Category: otc | Type: HUMAN OTC DRUG LABEL
Date: 20251104

ACTIVE INGREDIENTS: CALCIUM CARBONATE 750 mg/1 1
INACTIVE INGREDIENTS: ADIPIC ACID; D&C YELLOW NO. 10; DEXTROSE, UNSPECIFIED FORM; FD&C RED NO. 40; FD&C YELLOW NO. 6; MAGNESIUM STEARATE; MALTODEXTRIN; STARCH, CORN; SUCRALOSE

Extra Strength Antacid 750 Chewable Tablets

Active ingredient (per tablet)

Calcium Carbonate USP 750 mg

Purpose

Antacid

Uses

relieves:

• heartburn

• acid indigestion

• sour stomach

• upset stomach associated with these symptoms

Warnings

Ask a doctor or pharmacist before use if you arepresently taking a prescription drug. Antacids may interact with certain prescription drugs.

When using this product

- do not take more than 10 tablets in 24 hours
- If pregnant do not take more than 6 tablets in 24 hours
- do not use the maximum dosage for more than 2 weeks except under the advice and supervision of a doctor.

Directions

- adults and children 12 years of age and over:chew 2-4 tablets completely as symptoms occur, or as directed by a doctor. Do not swallow tablets whole.
- do not take for symptoms that persist for more than 2 weeks unless advised by a doctor

Other information

• each tablet contains:elemental calcium 300mg

• Store at room temperature. Keep the container tightly closed.

Inactive ingredients

adipic acid, D&C Yellow No. 10 Lake, dextrose, FD&C Red No. 40 Lake, FD&C Yellow No. 6 Lake, flavors, magnesium stearate, maltodextrin, starch, sucralose.

Questions ?

1-866-467-2748

Package/Label Principal Display Panel

NDC 11673-699-96

Compare to the active ingredient in Extra Strength Tums®

EXTRA STRENGTH

Calcium Carbonate 750 mg

Fast Relief of Upset Stomach, Heartburn and Acid Indigestion

TROPICAL FRUIT FLAVOR

Naturally and Artificially Flavored

96 Chewable Tablets

GLUTEN FREE

Dist.by Target Corp.

Mpls., MN 55403

© 2019 Target Brands, Inc.

*This product is not manufactured or distributed by GlaxoSmithKline LLC, owner of the registered trademark Tums®.

SAFETY SEALED: DO NOT USE IF PRINTED SEAL UNDER CAP IS TORN OR MISSING